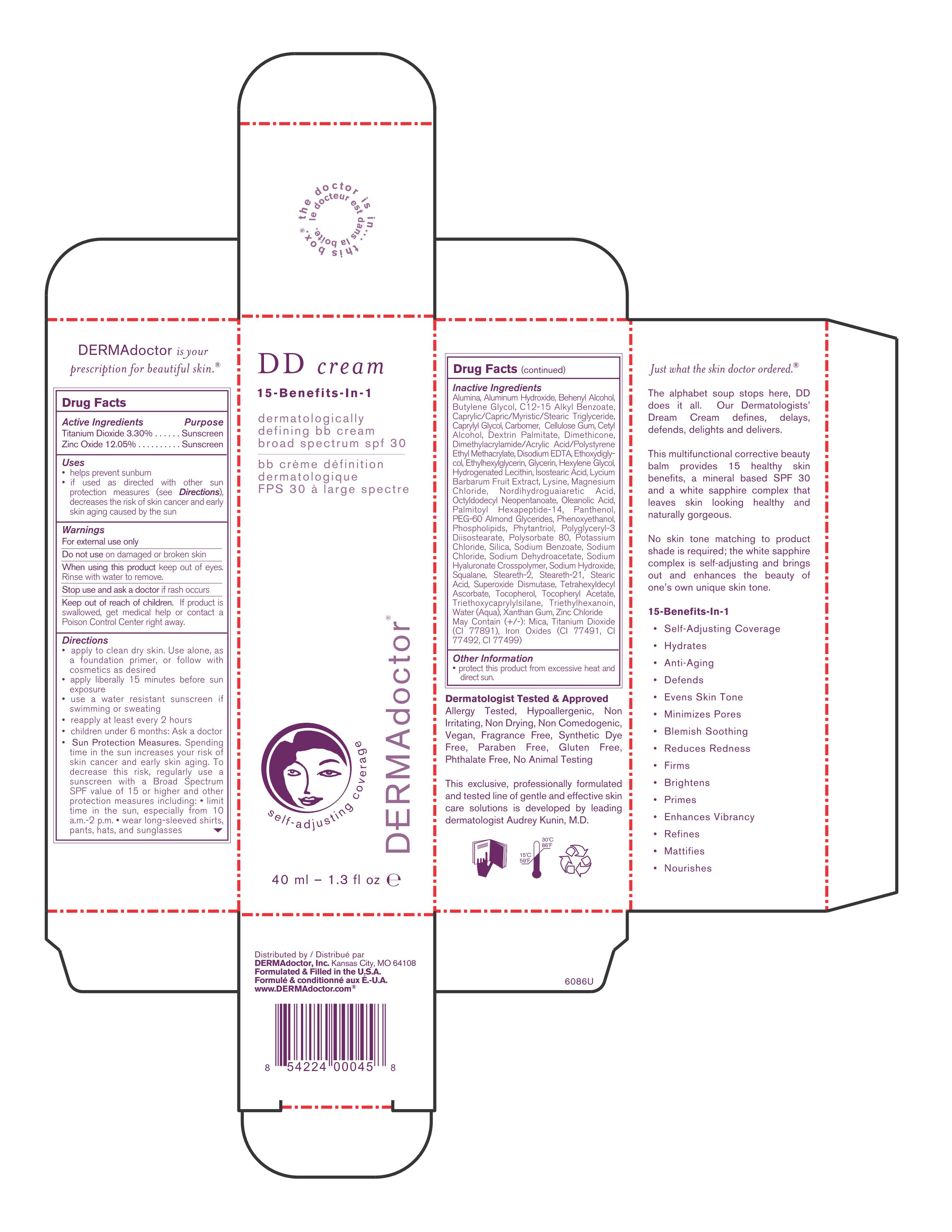 DRUG LABEL: DD Cream
NDC: 68715-458 | Form: CREAM
Manufacturer: DERMAdoctor, Inc.
Category: otc | Type: HUMAN OTC DRUG LABEL
Date: 20251016

ACTIVE INGREDIENTS: ZINC OXIDE 12.05 mg/100 mL; TITANIUM DIOXIDE 3.3 mg/100 mL
INACTIVE INGREDIENTS: MASOPROCOL; OLEANOLIC ACID; MUSKMELON; OMEGA-3 FATTY ACIDS; ALUMINUM OXIDE; DIETHYLENE GLYCOL MONOETHYL ETHER; LYCIUM BARBARUM FRUIT; PANTHENOL; LYSINE; MAGNESIUM CHLORIDE; ZINC CHLORIDE; .ALPHA.-TOCOPHEROL ACETATE; TOCOPHEROL; HYALURONATE SODIUM; DIMETHICONE; SILICON DIOXIDE; CARBOXYMETHYLCELLULOSE SODIUM; XANTHAN GUM; ETHYLHEXYLGLYCERIN; EDETATE DISODIUM; SODIUM BENZOATE; PHENOXYETHANOL; CAPRYLYL GLYCOL; MEDIUM-CHAIN TRIGLYCERIDES; TRIETHYLHEXANOIN; STEARIC ACID; ALKYL (C12-15) BENZOATE; OCTYLDODECYL NEOPENTANOATE; BUTYLENE GLYCOL; STEARETH-2; STEARETH-21; SQUALANE; ALUMINUM HYDROXIDE; POTASSIUM CHLORIDE; SODIUM CHLORIDE; SODIUM HYDROXIDE; SODIUM DEHYDROACETATE; MICA; HEXYLENE GLYCOL; TETRAHEXYLDECYL ASCORBATE; CETYL ALCOHOL; ISOSTEARIC ACID; DOCOSANOL; POLYGLYCERYL-3 DIISOSTEARATE; HYDROGENATED SOYBEAN LECITHIN; PHYTANTRIOL; TRIETHOXYCAPRYLYLSILANE; POLYSORBATE 80; PEG-60 ALMOND GLYCERIDES; GLYCERIN

DD Cream

Active Ingredients

Titanium Dioxide 3.30 % Dermadoctor - Sunscreen

Zinc Oxide 12.05 % Dermadoctor

Warnings

For external use only; do not use on damaged skin; keep out of eyes; keep out of reach of children – seek help if swallowed

Directions

Apply liberally 15 minutes before sun exposure.
Reapply at least every 2 hours.
Use a water-resistant sunscreen if swimming or sweating.
Children under 6 months: ask a doctor.

Inactive Ingredients

Alumina

Aluminum Hydroxide

Behenyl Alcohol

Butylene Glycol

C12-15 Alkyl Benzoate

Caprylic/Capric/Myristic/Stearic Triglyceride

Caprylyl Glycol

Carbomer

Cellulose Gum

Cetyl Alcohol

Dextrin Palmitate

Dimethicone

Dimethylacrylamide/Acrylic Acid/Polystyrene Ethyl Methacrylate

Disodium EDTA

Ethoxydiglycol

Ethylhexylglycerin

Glycerin

Hexylene Glycol

Hydrogenated Lecithin

Isostearic Acid

Lycium Barbarum Fruit Extract

Lysine

Magnesium Chloride

Nordihydroguaiaretic Acid

Octyldodecyl Neopentanoate

Oleanolic Acid

Palmitoyl Hexapeptide-14

Panthenol

PEG-60 Almond Glycerides

Phenoxyethanol

Phospholipids

Phytantriol

Polyglyceryl-3 Diisostearate

Polysorbate 80

Potassium Chloride

Silica

Sodium Benzoate

Sodium Chloride

Sodium Dehydroacetate

Sodium Hyaluronate Crosspolymer

Sodium Hydroxide

Squalane

Steareth-2

Steareth-21

Stearic Acid

Superoxide Dismutase

Tetrahexyldecyl Ascorbate

Tocopherol

Tocopheryl Acetate

Triethoxycaprylylsilane

Triethylhexanoin

Water (Aqua)

Xanthan Gum

Zinc Chloride

May Contain (+/-):

Mica

Titanium Dioxide (CI 77891)

Iron Oxides (CI 77491, CI 77492, CI 77499)

PURPOSE

Sunscreen

Keep out of reach of children. If swallowed, get medical help or contact a Poison Control Center right away.

DOSAGE AND ADMINISTRATION

Apply liberally 15 minutes before sun exposure.
Reapply at least every 2 hours.
Use a water-resistant sunscreen if swimming or sweating.
Children under 6 months: ask a doctor.

GERIATRIC USE

Helps prevent sunburn.
If used as directed with other sun protection measures, decreases the risk of skin cancer and early skin aging caused by the sun.

ROUTE, METHOD AND FREQUENCY OF ADMINISTRATION

Apply liberally 15 minutes before sun exposure.
Reapply at least every 2 hours.
Use a water-resistant sunscreen if swimming or sweating.
Children under 6 months: ask a doctor.

STATEMENT OF IDENTITY

Helps prevent sunburn.
If used as directed with other sun protection measures, decreases the risk of skin cancer and early skin aging caused by the sun.

INDICATIONS AND USAGE

Helps prevent sunburn.
If used as directed with other sun protection measures, decreases the risk of skin cancer and early skin aging caused by the sun.

40 ml Carton

DD cream

15-Benefits-In-1

dermatologically

defining bb cream with

broadspectrum spf 30

40 ml – 1.3 oz e

DD CREAM.jpg

DD Cream Principal Display Panel - 40ml Carton DD CREAM.jpg

PRINCIPAL DISPLAY PANEL - 40mL Carton

DERMAdoctor®

DD Cream

15-Benefits-In-1

dermatologically defining bb cream with broad spectrum spf 30

40 ml-1.3 fl oz

DD CREAM.jpg